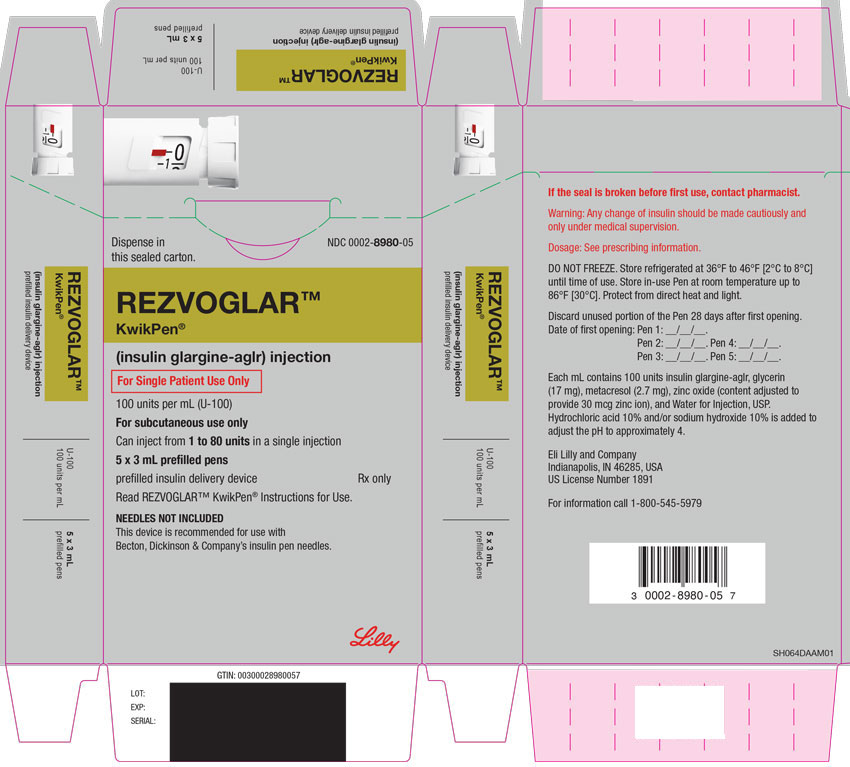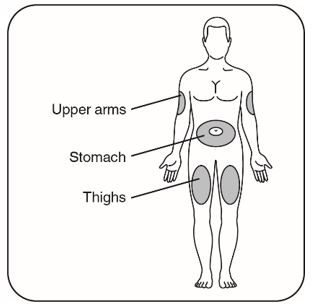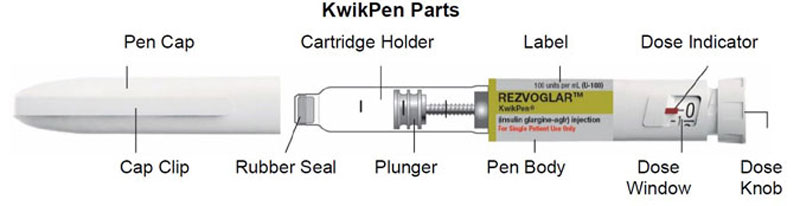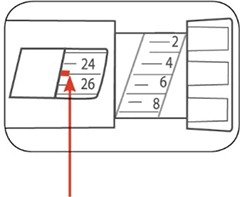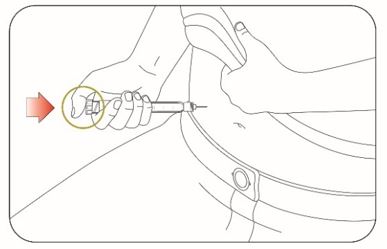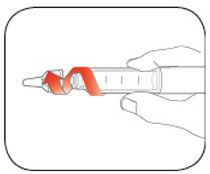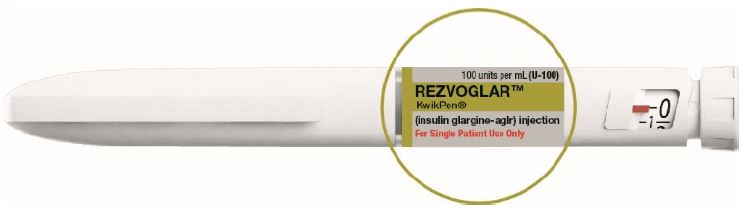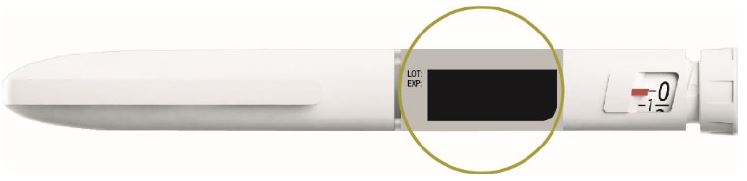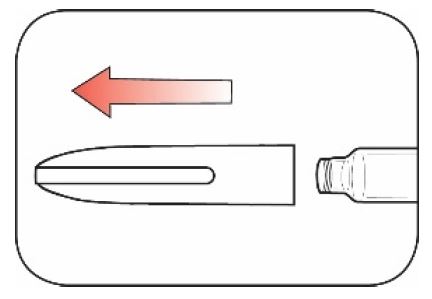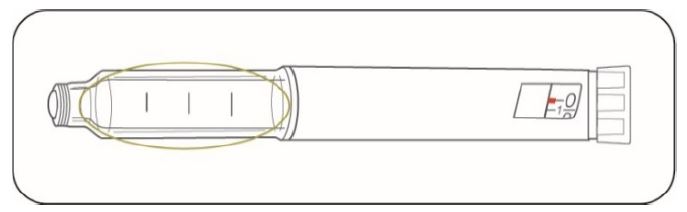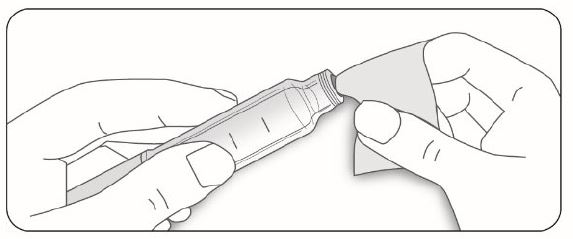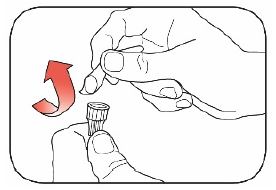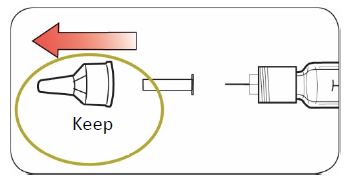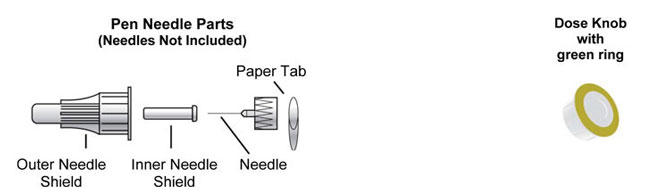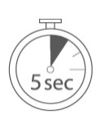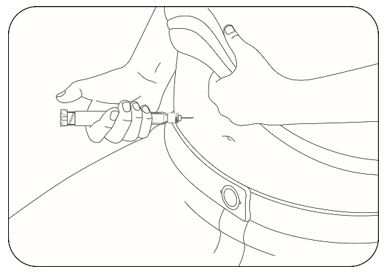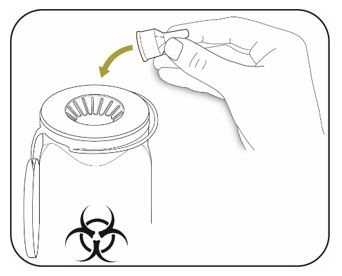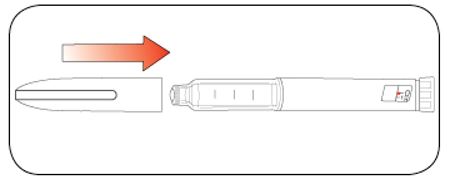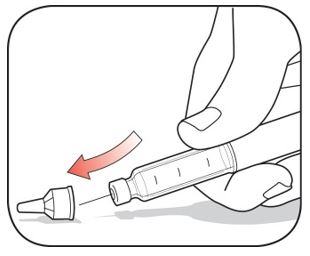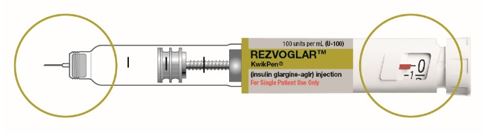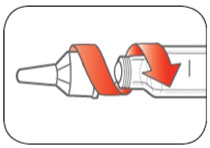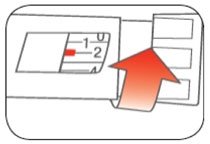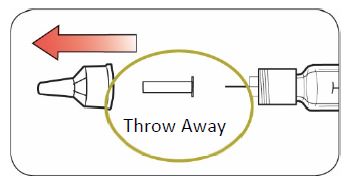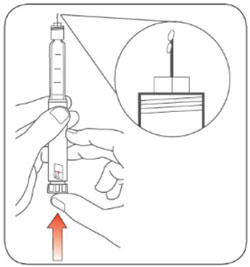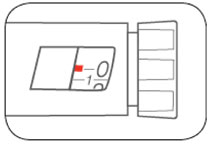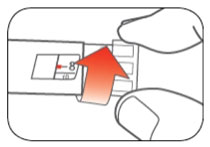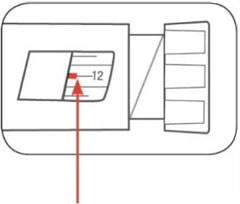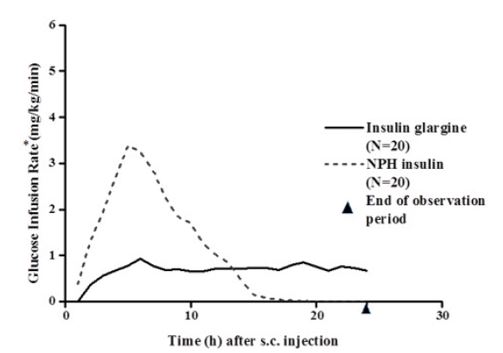 DRUG LABEL: Rezvoglar 
NDC: 0002-8980 | Form: INJECTION, SOLUTION
Manufacturer: Eli Lilly and Company
Category: prescription | Type: HUMAN PRESCRIPTION DRUG LABEL
Date: 20240809

ACTIVE INGREDIENTS: Insulin glargine 100 [iU]/1 mL
INACTIVE INGREDIENTS: Zinc oxide 0.03 mg/1 mL; Metacresol 2.7 mg/1 mL; Glycerin 17 mg/1 mL; Water; Hydrochloric acid; Sodium hydroxide

HIGHLIGHTS OF PRESCRIBING INFORMATION

These highlights do not include all the information needed to use REZVOGLAR safely and effectively. See full prescribing information for REZVOGLAR.
REZVOGLAR (insulin glargine-aglr) injection, for subcutaneous use
Initial U.S. Approval: 2021
REZVOGLAR (insulin glargine-aglr) is biosimilar [Biosimilar means that the biological product is approved based on data demonstrating that it is highly similar to an FDA-approved biological product, known as a reference product, and that there are no clinically meaningful differences between the biosimilar product and the reference product. Biosimilarity of Rezvoglar has been demonstrated for the condition(s) of use (e.g., indication(s), dosing regimen(s)), strength(s), dosage form(s), and route(s) of administration described in its Full Prescribing Information.] to LANTUS (insulin glargine)

1 INDICATIONS AND USAGE

REZVOGLAR™ is a long-acting human insulin analog indicated to improve glycemic control in adult and pediatric patients with diabetes mellitus. (1)

Limitations of Use:
Not recommended for the treatment of diabetic ketoacidosis. (1)

2 DOSAGE AND ADMINISTRATION

- Individualize dosage based on metabolic needs, blood glucose monitoring, glycemic control, type of diabetes, and prior insulin use. (2.2)
- Administer subcutaneously into the abdominal area, thigh, or deltoid once daily at any time of day, but at the same time every day. (2.1)
- Do not dilute or mix with any other insulin or solution. (2.1)
- Rotate injection sites to reduce the risk of lipodystrophy and localized cutaneous amyloidosis. (2.1)
- See Full Prescribing Information for the recommended starting dosage in patients with type 2 diabetes (2.3) and how to change to REZVOGLAR from other insulins (2.4)
- Closely monitor glucose when switching to REZVOGLAR and during initial weeks thereafter. (2.4)

3 DOSAGE FORMS AND STRENGTHS

Injection: 100 units/mL (U-100) available as:

- 3 mL single-patient-use REZVOGLAR™ KwikPen® prefilled pen (3)

4 CONTRAINDICATIONS

- During episodes of hypoglycemia. (4)
- Hypersensitivity to insulin glargine products or any of the excipients in REZVOGLAR. (4)

5 WARNINGS AND PRECAUTIONS

- Never share a REZVOGLAR KwikPen prefilled pen between patients, even if the needle is changed. (5.1)
- Hyperglycemia or hypoglycemia with changes in insulin regimen: Make changes to a patient's insulin regimen (e.g., insulin strength, manufacturer, type, injection site or method of administration) under close medical supervision with increased frequency of blood glucose monitoring. (5.2)
- Hypoglycemia: May be life-threatening. Increase frequency of glucose monitoring with changes to: insulin dosage, concomitant drugs, meal pattern, physical activity; and in patients with renal or hepatic impairment and hypoglycemia unawareness. (5.3)
- Hypoglycemia due to Medication Errors: Accidental mix-ups between insulin products can occur. Instruct patients to check insulin labels before injection. (5.4)
- Hypersensitivity reactions: Severe, life-threatening, generalized allergy, including anaphylaxis, can occur. Discontinue REZVOGLAR. Monitor and treat if indicated. (5.5)
- Hypokalemia: May be life-threatening. Monitor potassium levels in patients at risk of hypokalemia and treat if indicated. (5.6)
- Fluid retention and heart failure with concomitant use of thiazolidinediones (TZDs): Observe for signs and symptoms of heart failure; consider dosage reduction or discontinuation of TZD if heart failure occurs. (5.7)

6 ADVERSE REACTIONS

Adverse reactions commonly associated with insulin glargine products include hypoglycemia, allergic reactions, injection site reactions, lipodystrophy, pruritus, rash, edema, and weight gain. (6.1)

To report SUSPECTED ADVERSE REACTIONS, contact Eli Lilly and Company at 1-800-LillyRx (1-800-545-5979) or FDA at 1-800-FDA-1088 or www.fda.gov/medwatch.

7 DRUG INTERACTIONS

- Drugs that Affect Glucose Metabolism: Adjustment of insulin dosage may be needed. (7)
- Antiadrenergic Drugs (e.g., beta-blockers, clonidine, guanethidine, and reserpine): Signs and symptoms of hypoglycemia may be reduced or absent. (7)

FULL PRESCRIBING INFORMATION

1 INDICATIONS AND USAGE

REZVOGLAR™ is indicated to improve glycemic control in adult and pediatric patients with diabetes mellitus.

Limitations of Use

REZVOGLAR is not recommended for the treatment of diabetic ketoacidosis.

2 DOSAGE AND ADMINISTRATION

2.1 Important Administration Instructions

- Always check insulin labels before administration [see Warnings and Precautions (5.4)].
- Visually inspect REZVOGLAR KwikPen prefilled pens for particulate matter and discoloration prior to administration. Only use if the solution is clear and colorless with no visible particles.
- Administer REZVOGLAR subcutaneously into the abdominal area, thigh, or deltoid, and rotate injection sites within the same region from one injection to the next to reduce the risk of lipodystrophy and localized cutaneous amyloidosis. Do not inject into areas of lipodystrophy or localized cutaneous amyloidosis [see Warnings and Precautions (5.2), and Adverse Reactions (6)].
- During changes to a patient's insulin regimen, increase the frequency of blood glucose monitoring [see Warnings and Precautions (5.2)].
- Do not administer intravenously or via an insulin pump.
- Do not dilute or mix REZVOGLAR with any other insulin or solution.
- The REZVOGLAR KwikPen prefilled pen dials in 1-unit increments.
- Use REZVOGLAR KwikPen prefilled pen with caution in patients with visual impairment who may rely on audible clicks to dial their dose.

2.2 General Dosing Instructions

- Administer REZVOGLAR subcutaneously once daily at any time of day but at the same time every day.
- Individualize and adjust the dosage of REZVOGLAR based on the patient's metabolic needs, blood glucose monitoring results and glycemic control goal.
- Dosage adjustments may be needed with changes in physical activity, changes in meal patterns (i.e., macronutrient content or timing of food intake), during acute illness, or changes in renal or hepatic function. Dosage adjustments should only be made under medical supervision with appropriate glucose monitoring [see Warnings and Precautions (5.2)].
- In patients with type 1 diabetes, REZVOGLAR must be used concomitantly with short-acting insulin.

2.3 Initiation of REZVOGLAR Therapy

Recommended Starting Dosage in Patients with Type 1 Diabetes

The recommended starting dosage of REZVOGLAR in patients with type 1 diabetes is approximately one-third of the total daily insulin requirements. Use short-acting, premeal insulin to satisfy the remainder of the daily insulin requirements.

Recommended Starting Dosage in Patients with Type 2 Diabetes

The recommended starting dosage of REZVOGLAR in patients with type 2 diabetes who are not currently treated with insulin is 0.2 units/kg or up to 10 units once daily.

2.4 Switching to REZVOGLAR from Other Insulin Therapies

Dosage adjustments are recommended to lower the risk of hypoglycemia when switching patients to REZVOGLAR from other insulin therapies [see Warnings and Precautions (5.3)]. When switching from:

- Once-daily insulin glargine, 300 units/mL, to once-daily REZVOGLAR (100 units/mL), the recommended starting REZVOGLAR dosage is 80% of the insulin glargine, 300 units/mL dosage that is being discontinued.
- Once-daily NPH insulin to once-daily REZVOGLAR, the recommended starting REZVOGLAR dosage is the same as the dosage of NPH that is being discontinued.
- Twice-daily NPH insulin to once-daily REZVOGLAR, the recommended starting REZVOGLAR dosage is 80% of the total NPH dosage that is being discontinued.

3 DOSAGE FORMS AND STRENGTHS

Injection: 100 units/mL (U-100) a clear and colorless solution available as:

- 3 mL single-patient-use REZVOGLAR KwikPen prefilled pen.

4 CONTRAINDICATIONS

REZVOGLAR is contraindicated:

- during episodes of hypoglycemia [see Warnings and Precautions (5.3)].
- in patients with hypersensitivity to insulin glargine products or any of the excipients in REZVOGLAR [see Warnings and Precautions (5.5)].

5 WARNINGS AND PRECAUTIONS

5.1 Never Share a REZVOGLAR KwikPen Prefilled Pen Between Patients

REZVOGLAR KwikPen prefilled pens must never be shared between patients, even if the needle is changed. Sharing poses a risk for transmission of blood-borne pathogens.

5.2 Hyperglycemia or Hypoglycemia with Changes in Insulin Regimen

Changes in an insulin regimen (e.g., insulin strength, manufacturer, type, injection site or method of administration) may affect glycemic control and predispose to hypoglycemia [see Warnings and Precautions (5.3)] or hyperglycemia. Repeated insulin injections into areas of lipodystrophy or localized cutaneous amyloidosis have been reported to result in hyperglycemia; and a sudden change in the injection site (to unaffected area) has been reported to result in hypoglycemia [see Adverse Reactions (6)].

Make any changes to a patient's insulin regimen under close medical supervision with increased frequency of blood glucose monitoring. Advise patients who have repeatedly injected into areas of lipodystrophy or localized cutaneous amyloidosis to change the injection site to unaffected areas and closely monitor for hypoglycemia. For patients with type 2 diabetes, dosage adjustments of concomitant oral and antidiabetic products may be needed.

5.3 Hypoglycemia

Hypoglycemia is the most common adverse reaction associated with insulins, including insulin glargine products. Severe hypoglycemia can cause seizures, may be life-threatening or cause death. Hypoglycemia can impair concentration ability and reaction time; this may place the patient and others at risk in situations where these abilities are important (e.g., driving or operating other machinery).

Hypoglycemia can happen suddenly and symptoms may differ in each patient and change over time in the same patient. Symptomatic awareness of hypoglycemia may be less pronounced in patients with longstanding diabetes, in patients with diabetic neuropathy, using drugs that block the sympathetic nervous system (e.g., beta-blockers) [see Drug Interactions (7)], or who experience recurrent hypoglycemia.

The long-acting effect of insulin glargine products may delay recovery from hypoglycemia.

Risk Factors for Hypoglycemia

The risk of hypoglycemia after an injection is related to the duration of action of the insulin and, in general, is highest when the glucose lowering effect of the insulin is maximal. As with all insulins, the glucose lowering effect time course of insulin glargine products may vary in different patients or at different times in the same patient and depends on many conditions, including the area of injection as well as the injection site blood supply and temperature [see Clinical Pharmacology (12.2)]. Other factors which may increase the risk of hypoglycemia include changes in meal pattern (e.g., macronutrient content or timing of meals), changes in level of physical activity, or changes to concomitant drugs [see Drug Interactions (7)]. Patients with renal or hepatic impairment may be at higher risk of hypoglycemia [see Use in Specific Populations (8.6, 8.7)].

Risk Mitigation Strategies for Hypoglycemia

Patients and caregivers must be educated to recognize and manage hypoglycemia. Self-monitoring of blood glucose plays an essential role in the prevention and management of hypoglycemia. In patients at higher risk for hypoglycemia and patients who have reduced symptomatic awareness of hypoglycemia, increased frequency of blood glucose monitoring is recommended.

5.4 Hypoglycemia Due to Medication Errors

Accidental mix-ups among insulin products have been reported. To avoid medication errors between REZVOGLAR and other insulins, instruct patients to always check the insulin label before each injection [see Adverse Reactions (6.3)].

5.5 Hypersensitivity Reactions

Severe, life-threatening, generalized allergy, including anaphylaxis, can occur with insulins, including insulin glargine products [see Adverse Reactions (6.1)]. If hypersensitivity reactions occur, discontinue REZVOGLAR; treat per standard of care and monitor until symptoms and signs resolve. REZVOGLAR is contraindicated in patients who have had hypersensitivity reactions to insulin glargine products or one of the excipients in REZVOGLAR.

5.6 Hypokalemia

All insulins, including insulin glargine products, cause a shift in potassium from the extracellular to intracellular space, possibly leading to hypokalemia. Untreated hypokalemia may cause respiratory paralysis, ventricular arrhythmia, and death. Monitor potassium levels in patients at risk for hypokalemia if indicated (e.g., patients using potassium-lowering medications, patients taking medications sensitive to serum potassium concentrations).

5.7 Fluid Retention and Heart Failure with Concomitant Use of PPAR-gamma Agonists

Thiazolidinediones (TZDs), which are peroxisome proliferator-activated receptor (PPAR)-gamma agonists, can cause dose-related fluid retention, when used in combination with insulin. Fluid retention may lead to or exacerbate heart failure. Patients treated with insulin, including REZVOGLAR, and a PPAR-gamma agonist should be observed for signs and symptoms of heart failure. If heart failure develops, it should be managed according to current standards of care, and discontinuation or dose reduction of the PPAR-gamma agonist must be considered.

6 ADVERSE REACTIONS

The following adverse reactions are discussed elsewhere:

- Hyperglycemia or Hypoglycemia with Changes in Insulin Regimen [see Warnings and Precautions (5.2)]
- Hypoglycemia [see Warnings and Precautions (5.3)].
- Hypoglycemia Due to Medication Errors [see Warnings and Precautions (5.4)].
- Hypersensitivity Reactions [see Warnings and Precautions (5.5)].
- Hypokalemia [see Warnings and Precautions (5.6)].

6.1 Clinical Trials Experience

Because clinical trials are conducted under widely varying conditions, adverse reaction rates observed in clinical trials of a drug cannot be directly compared to rates in the clinical trial of another drug and may not reflect the rates observed in practice.

The data in Table 1 reflect the exposure of 2,327 patients with type 1 diabetes to insulin glargine or NPH in Studies A, B, C, and D [see Clinical Studies (14.2)]. The type 1 diabetes population had the following characteristics: the mean age was 39 years, 54% were male, and mean body mass index (BMI) was 25.1 kg/m^2. Ninety-seven percent were White, 2% were Black or African American and less than 1% were Asian. Approximately 3% of the patients in studies B and C were Hispanic.

The data in Table 2 reflect the exposure of 1,563 patients with type 2 diabetes to insulin glargine or NPH in Studies E, F, and G [see Clinical Studies (14.3)]. The type 2 diabetes population had the following characteristics: the mean age was 59 years, 58% were male, and mean BMI was 29.2 kg/m^2. Eighty-seven percent were White, 8% were Black or African American and 3% were Asian. Approximately 9% of patients in Study F were Hispanic.

The frequencies of adverse reactions during insulin glargine clinical studies in patients with type 1 diabetes mellitus and type 2 diabetes mellitus are listed in the tables below (Tables 1, 2, 3, and 4).

Table 1: Adverse Reactions Occurring ≥5% in Pooled Clinical Studies up to 28 Weeks Duration in Adults with Type 1 Diabetes
 | Insulin Glargine, % (n=1,257) | NPH, % (n=1,070)
Upper respiratory tract infection | 22.4 | 23.1
Infection* | 9.4 | 10.3
Accidental injury | 5.7 | 6.4
Headache | 5.5 | 4.7
* Body system not specified

Table 2: Adverse Reactions Occurring ≥5% in Pooled Clinical Studies up to 1 Year Duration in Adults with Type 2 Diabetes
 | Insulin Glargine, % (n=849) | NPH, % (n=714)
Upper respiratory tract infection | 11.4 | 13.3
Infection* | 10.4 | 11.6
Retinal vascular disorder | 5.8 | 7.4
* Body system not specified

Table 3: Adverse Reactions Occurring ≥10% in a 5-Year Study of Adults with Type 2 Diabetes
 | Insulin Glargine, % (n=514) | NPH, % (n=503)
Upper respiratory tract infection | 29.0 | 33.6
Edema peripheral | 20.0 | 22.7
Hypertension | 19.6 | 18.9
Influenza | 18.7 | 19.5
Sinusitis | 18.5 | 17.9
Cataract | 18.1 | 15.9
Bronchitis | 15.2 | 14.1
Arthralgia | 14.2 | 16.1
Pain in extremity | 13.0 | 13.1
Back pain | 12.8 | 12.3
Cough | 12.1 | 7.4
Urinary tract infection | 10.7 | 10.1
Diarrhea | 10.7 | 10.3
Depression | 10.5 | 9.7
Headache | 10.3 | 9.3

Table 4: Adverse Reactions Occurring ≥5% in a 28-Week Clinical Study in Pediatric Patients with Type 1 Diabetes
 | Insulin Glargine,% (n=174) | NPH, % (n=175)
Infection* | 13.8 | 17.7
Upper respiratory tract infection | 13.8 | 16.0
Pharyngitis | 7.5 | 8.6
Rhinitis | 5.2 | 5.1
* Body system not specified

Severe Hypoglycemia

Hypoglycemia was the most commonly observed adverse reaction in patients treated with insulin glargine. Tables 5, 6, and 7 summarize the incidence of severe hypoglycemia in insulin glargine clinical studies. Severe symptomatic hypoglycemia was defined as an event with symptoms consistent with hypoglycemia requiring the assistance of another person and associated with either a blood glucose below 50 mg/dL (≤56 mg/dL in the 5-year study and ≤36 mg/dL in the ORIGIN study) or prompt recovery after oral carbohydrate, intravenous glucose or glucagon administration.

Percentages of insulin glargine-treated adult patients who experienced severe symptomatic hypoglycemia in the insulin glargine clinical studies [see Clinical Studies (14)] were comparable to percentages of NPH-treated patients for all treatment regimens (see Tables 5 and 6). In the pediatric clinical study, pediatric patients with type 1 diabetes had a higher incidence of severe symptomatic hypoglycemia in the two treatment groups compared to the adult studies with type 1 diabetes.

Table 5: Severe Symptomatic Hypoglycemia in Patients with Type 1 Diabetes
 | Study A Type 1 Diabetes Adults 28 weeks In combination with regular insulin |  | Study B Type 1 Diabetes Adults 28 weeks In combination with regular insulin |  | Study C Type 1 Diabetes Adults 16 weeks In combination with insulin lispro |  | Study D Type 1 Diabetes Pediatrics 26 weeks In combination with regular insulin
 | Insulin Glargine n=292 | NPH n=293 | Insulin Glargine n=264 | NPH n=270 | Insulin Glargine n=310 | NPH n=309 | Insulin Glargine n=174 | NPH n=175
Percent of patients | 10.6 | 15.0 | 8.7 | 10.4 | 6.5 | 5.2 | 23.0 | 28.6

Table 6: Severe Symptomatic Hypoglycemia in Patients with Type 2 Diabetes
 | Study E Type 2 Diabetes Adults 52 weeks In combination with oral agents |  | Study F Type 2 Diabetes Adults 28 weeks In combination with regular insulin |  | Study G Type 2 Diabetes Adults 5 years In combination with regular insulin
 | Insulin Glargine n=289 | NPH n=281 | Insulin Glargine n=259 | NPH n=259 | Insulin Glargine n=513 | NPH n=504
Percent of patients | 1.7 | 1.1 | 0.4 | 2.3 | 7.8 | 11.9

Table 7 displays the proportion of patients who experienced severe symptomatic hypoglycemia in the insulin glargine and Standard Care groups in the ORIGIN study [see Clinical Studies (14)].

Table 7: Severe Symptomatic Hypoglycemia in the ORIGIN Study
 | ORIGIN Study Median duration of follow-up: 6.2 years
 | Insulin Glargine (n=6,231) | Standard Care (n=6,273)
Percent of patients | 5.6 | 1.8

Peripheral Edema

Some patients taking insulin glargine products have experienced sodium retention and edema, particularly if previously poor metabolic control was improved by intensified insulin therapy.

Lipodystrophy

Administration of insulin subcutaneously, including insulin glargine products, has resulted in lipoatrophy (depression in the skin) or lipohypertrophy (enlargement or thickening of tissue) in some patients [see Dosage and Administration (2.2)].

Insulin Initiation and Intensification of Glucose Control

Intensification or rapid improvement in glucose control has been associated with a transitory, reversible ophthalmologic refraction disorder, worsening of diabetic retinopathy, and acute painful peripheral neuropathy. However, long-term glycemic control decreases the risk of diabetic retinopathy and neuropathy.

Weight Gain

Weight gain has occurred with insulin including insulin glargine products and has been attributed to the anabolic effects of insulin and the decrease in glucosuria.

Hypersensitivity Reactions

Local Reactions

Patients taking insulin glargine experienced injection site reactions, including redness, pain, itching, urticaria, edema, and inflammation. In clinical studies in adult patients, there was a higher incidence of injection site pain in insulin glargine-treated patients (2.7%) compared to NPH insulin-treated patients (0.7%). The reports of pain at the injection site did not result in discontinuation of therapy.

Systemic Reactions

Severe, life-threatening, generalized allergy, including anaphylaxis, generalized skin reactions, angioedema, bronchospasm, hypotension, and shock have occurred with insulin, including insulin glargine products and may be life threatening.

6.2 Immunogenicity

As with all therapeutic proteins, there is potential for immunogenicity. The detection of antibody formation is highly dependent on the sensitivity and specificity of the assay. Additionally, the observed incidence of antibody (including neutralizing antibody) positivity in an assay may be influenced by several factors, including assay methodology, sample handling, timing of sample collection, concomitant medications, and underlying disease. For these reasons, comparison of the incidence of antibodies in the studies described below with the incidence of antibodies in other studies or to other insulin glargine products may be misleading. All insulin products can elicit the formation of insulin antibodies. The presence of such insulin antibodies may increase or decrease the efficacy of insulin and may require adjustment of the insulin dose. In clinical studies of insulin glargine, increases in titers of antibodies to insulin were observed in NPH insulin and insulin glargine treatment groups with similar incidences.

6.3 Postmarketing Experience

The following adverse reactions have been identified during postapproval use of insulin glargine products. Because these reactions are reported voluntarily from a population of uncertain size, it is not always possible to reliably estimate their frequency or establish a causal relationship to drug exposure.

Medication errors have been reported in which rapid-acting insulins and other insulins, have been accidentally administered instead of insulin glargine products.

Localized cutaneous amyloidosis at the injection site has occurred. Hyperglycemia has been reported with repeated insulin injections into areas of localized cutaneous amyloidosis; hypoglycemia has been reported with a sudden change to an unaffected injection site.

7 DRUG INTERACTIONS

Table 8 includes clinically significant drug interactions with REZVOGLAR.

Table 8: Clinically Significant Drug Interactions with REZVOGLAR
Drugs that May Increase the Risk of Hypoglycemia
Drugs: | Antidiabetic agents, ACE inhibitors, angiotensin II receptor blocking agents, disopyramide, fibrates, fluoxetine, monoamine oxidase inhibitors, pentoxifylline, pramlintide, salicylates, somatostatin analogs (e.g., octreotide), sulfonamide antibiotics. GLP-1 receptor agonists, DPP-4 inhibitors, and SGLT-2 inhibitors.
Intervention: | Dosage reductions and increased frequency of glucose monitoring may be required when REZVOGLAR is coadministered with these drugs.
Drugs that May Decrease the Blood Glucose Lowering Effect of REZVOGLAR
Drugs: | Atypical antipsychotics (e.g., olanzapine and clozapine), corticosteroids, danazol, diuretics, estrogens, glucagon, isoniazid, niacin, oral contraceptives, phenothiazines, progestogens (e.g., in oral contraceptives), protease inhibitors, somatropin, sympathomimetic agents (e.g., albuterol, epinephrine, terbutaline), and thyroid hormones.
Intervention: | Dosage increases and increased frequency of glucose monitoring may be required when REZVOGLAR is coadministered with these drugs.
Drugs that May Increase or Decrease the Blood Glucose Lowering Effect of REZVOGLAR
Drugs: | Alcohol, beta-blockers, clonidine, and lithium salts. Pentamidine may cause hypoglycemia, which may sometimes be followed by hyperglycemia.
Intervention: | Dosage adjustment and increased frequency of glucose monitoring may be required when REZVOGLAR is coadministered with these drugs.
Drugs that May Blunt Signs and Symptoms of Hypoglycemia
Drugs: | Beta-blockers, clonidine, guanethidine, and reserpine.
Intervention: | Increased frequency of glucose monitoring may be required when REZVOGLAR is coadministered with these drugs.

8 USE IN SPECIFIC POPULATIONS

8.1 Pregnancy

Risk Summary

Published studies with use of insulin glargine products during pregnancy have not reported a clear association with insulin glargine products and adverse developmental outcomes (see Data). There are risks to the mother and fetus associated with poorly controlled diabetes in pregnancy (see Clinical Considerations).

Rats and rabbits were exposed to insulin glargine in animal reproduction studies during organogenesis, respectively 50 times and 10 times the human subcutaneous dosage of 0.2 units/kg/day. Overall, the effects of insulin glargine did not generally differ from those observed with regular human insulin (see Data).

In the U.S. general population, the estimated background risk of major birth defects and miscarriage in clinically recognized pregnancies is 2% to 4% and 15% to 20%, respectively. The estimated background risk of major birth defects is 6% to 10% in women with pregestational diabetes with a peri-conceptional HbA1c >7 and has been reported to be as high as 20% to 25% in women with a peri-conceptional HbA1c >10. The estimated background risk of miscarriage for the indicated population is unknown.

Clinical Considerations

Disease-Associated Maternal and/or Embryo-fetal Risk

Hypoglycemia and hyperglycemia occur more frequently during pregnancy in patients with pre-gestational diabetes. Poorly controlled diabetes in pregnancy increases the maternal risk for diabetic ketoacidosis, preeclampsia, spontaneous abortions, preterm delivery, and delivery complications. Poorly controlled diabetes increases the fetal risk for major birth defects, stillbirth, and macrosomia-related morbidity.

Data

Human Data

Published data do not report a clear association with insulin glargine products and major birth defects, miscarriage, or adverse maternal or fetal outcomes when insulin glargine is used during pregnancy. However, these studies cannot definitely establish the absence of any risk because of methodological limitations including small sample size and some lacking comparator groups.

Animal Data

Subcutaneous reproduction and teratology studies have been performed with insulin glargine and regular human insulin in rats and Himalayan rabbits. Insulin glargine was given to female rats before mating, during mating, and throughout pregnancy at doses up to 0.36 mg/kg/day, which is approximately 50 times the recommended human subcutaneous starting dosage of 0.2 units/kg/day (0.007 mg/kg/day), on a mg/kg basis. In rabbits, doses of 0.072 mg/kg/day, which is approximately 10 times the recommended human subcutaneous starting dosage of 0.2 units/kg/day on a mg/kg basis, were administered during organogenesis. The effects of insulin glargine did not generally differ from those observed with regular human insulin in rats or rabbits. However, in rabbits, five fetuses from two litters of the high-dose group exhibited dilation of the cerebral ventricles. Fertility and early embryonic development appeared normal.

8.2 Lactation

Risk Summary

There are either no or only limited data on the presence of insulin glargine products in human milk, the effects on the breastfed infant, or the effects on milk production. Endogenous insulin is present in human milk. The developmental and health benefits of breastfeeding should be considered along with the mother's clinical need for REZVOGLAR and any potential adverse effects on the breastfed child from REZVOGLAR or from the underlying maternal condition.

8.4 Pediatric Use

The safety and effectiveness of REZVOGLAR to improve glycemic control in pediatric patients with diabetes mellitus have been established. Use of REZVOGLAR for this indication is supported by evidence from an adequate and well-controlled study (Study D) in 174 insulin glargine-treated pediatric patients aged 6 to 15 years with type 1 diabetes mellitus, and from adequate and well-controlled studies of insulin glargine in adults with diabetes mellitus [see Clinical Pharmacology (12.3), Clinical Studies (14.2)].

In the pediatric clinical study, pediatric patients with type 1 diabetes had a higher incidence of severe symptomatic hypoglycemia compared to the adults in studies with type 1 diabetes [see Adverse Reactions (6.1)].

8.5 Geriatric Use

Of the total number of subjects in controlled clinical studies of patients with type 1 and type 2 diabetes who were treated with insulin glargine, 15% (n=316) were ≥65 years of age and 2% (n=42) were ≥75 years of age. No overall differences in safety or effectiveness of insulin glargine have been observed between patients 65 years of age and older and younger adult patients.

Nevertheless, caution should be exercised when REZVOGLAR is administered to geriatric patients. In geriatric patients with diabetes, the initial dosing, dosage increments, and maintenance dosage should be conservative to avoid hypoglycemic reactions. Hypoglycemia may be difficult to recognize in geriatric patients.

8.6 Renal Impairment

The effect of kidney impairment on the pharmacokinetics of insulin glargine products has not been studied. Some studies with human insulin have shown increased circulating levels of insulin in patients with kidney failure. Frequent glucose monitoring and dosage adjustment may be necessary for REZVOGLAR in patients with kidney impairment [see Warnings and Precautions (5.3)].

8.7 Hepatic Impairment

The effect of hepatic impairment on the pharmacokinetics of insulin glargine products has not been studied. Frequent glucose monitoring and dosage adjustment may be necessary for REZVOGLAR in patients with hepatic impairment [see Warnings and Precautions (5.3)].

10 OVERDOSAGE

Excess insulin administration may cause hypoglycemia and hypokalemia [see Warnings and Precautions (5.3, 5.6)].

Mild episodes of hypoglycemia can usually be treated with oral carbohydrates. Lowering the insulin dosage, and adjustments in meal patterns or exercise may be needed.

More severe episodes of hypoglycemia with coma, seizure, or neurologic impairment may be treated with glucagon for emergency use or concentrated intravenous glucose. After apparent clinical recovery from hypoglycemia, continued observation and additional carbohydrate intake may be necessary to avoid recurrence of hypoglycemia. Hypokalemia must be corrected appropriately.

11 DESCRIPTION

Insulin glargine-aglr is a long-acting human insulin analog produced by recombinant DNA technology utilizing a non-pathogenic laboratory strain of Escherichia coli (K12). Insulin glargine-aglr differs from human insulin in that the amino acid asparagine at position A21 is replaced by glycine and two arginines are added to the C-terminus of the B-chain. Insulin glargine-aglr has a molecular weight of 6063 Da.

REZVOGLAR (insulin glargine-aglr) injection is a sterile, clear and colorless solution for subcutaneous use in a 3 mL single-patient use prefilled pen (REZVOGLAR KwikPen).

Prefilled Pen (REZVOGLAR KwikPen): Each mL contains 100 units of insulin glargine-aglr and the inactive ingredients: glycerin (17 mg), metacresol (2.7 mg), zinc oxide (content adjusted to provide 30 mcg zinc ion), and Water for Injection, USP.

The pH is adjusted by addition of aqueous solutions of hydrochloric acid 10% and/or sodium hydroxide 10%. REZVOGLAR has a pH of approximately 4.

12 CLINICAL PHARMACOLOGY

12.1 Mechanism of Action

The primary activity of insulin, including insulin glargine products, is regulation of glucose metabolism. Insulin and its analogs lower blood glucose by stimulating peripheral glucose uptake, especially by skeletal muscle and fat, and by inhibiting hepatic glucose production. Insulin inhibits lipolysis and proteolysis, and enhances protein synthesis.

12.2 Pharmacodynamics

In clinical studies, the glucose-lowering effect on a molar basis (i.e., when given at the same doses) of intravenous insulin glargine is approximately the same as that for human insulin. Figure 1 shows results from a study in patients with type 1 diabetes conducted for a maximum of 24 hours after subcutaneous injection of insulin glargine or NPH insulin. The median time between subcutaneous injection and the end of pharmacological effect was 14.5 hours (range: 9.5 to 19.3 hours) for NPH insulin, and 24 hours (range: 10.8 to >24 hours) (24 hours was the end of the observation period) for insulin glargine.

Figure 1: Glucose-Lowering Effect Over 24 Hours in Patients with Type 1 Diabetes

* Determined as amount of glucose infused to maintain constant plasma glucose levels

The duration of action after abdominal, deltoid, or thigh subcutaneous administration of insulin glargine was similar. The time course of action of insulins, including insulin glargine products, may vary between patients and within the same patient.

12.3 Pharmacokinetics

Absorption

After subcutaneous injection of insulin glargine in healthy subjects and in patients with diabetes, the insulin serum concentrations indicated a slower, more prolonged absorption and a relatively constant concentration/time profile over 24 hours with no pronounced peak in comparison to NPH insulin.

Elimination

Metabolism

A metabolism study in humans indicates that insulin glargine is partly metabolized at the carboxyl terminus of the B chain in the subcutaneous depot to form two active metabolites with in vitro activity similar to that of human insulin, M1 (21A-Gly-insulin) and M2 (21A-Gly-des-30B-Thr-insulin). Unchanged drug and these degradation products are also present in the circulation.

Specific Populations

Age, Race, Body Mass Index, and Gender

Effect of age, race, body mass index (BMI), and gender on the pharmacokinetics of insulin glargine products has not been evaluated. However, in controlled clinical studies in adults (n=3,890) and a controlled clinical study in pediatric patients (n=349), subgroup analyses based on age, race, BMI, and gender did not show differences in safety and efficacy between insulin glargine and NPH insulin [see Clinical Studies (14)].

13 NONCLINICAL TOXICOLOGY

13.1 Carcinogenesis, Mutagenesis, Impairment of Fertility

In mice and rats, standard two-year carcinogenicity studies with insulin glargine were performed at doses up to 0.455 mg/kg, which was for the rat approximately 65 times the recommended human subcutaneous starting dosage of 0.2 units/kg/day (0.007 mg/kg/day) on a mg/kg basis. Histiocytomas were found at injection sites in male rats and mice in acid vehicle containing groups and are considered a response to chronic tissue irritation and inflammation in rodents. These tumors were not found in female animals, in saline control, or insulin comparator groups using a different vehicle.

Insulin glargine was not mutagenic in tests for detection of gene mutations in bacteria and mammalian cells (Ames- and HGPRT-test) and in tests for detection of chromosomal aberrations (cytogenetics in vitro in V79 cells and in vivo in Chinese hamsters).

In a combined fertility and prenatal and postnatal study of insulin glargine in male and female rats at subcutaneous doses up to 0.36 mg/kg/day, which was approximately 50 times the recommended human subcutaneous starting dose of 0.2 units/kg/day (0.007 mg/kg/day) maternal toxicity due to dose-dependent hypoglycemia, including some deaths, was observed. Consequently, a reduction of the rearing rate occurred in the high-dose group only. Similar effects were observed with NPH insulin.

14 CLINICAL STUDIES

14.1 Overview of Clinical Studies

The safety and effectiveness of insulin glargine given once-daily at bedtime was compared to that of once-daily and twice-daily NPH insulin in open-label, randomized, active-controlled, parallel studies of 2,327 adult patients and 349 pediatric patients with type 1 diabetes mellitus and 1,563 adult patients with type 2 diabetes mellitus (see Tables 9 - 11). In general, the reduction in glycated hemoglobin (HbA1c) with insulin glargine was similar to that with NPH insulin.

14.2 Clinical Studies in Adult and Pediatric Patients with Type 1 Diabetes

Adult Patients with Type 1 Diabetes

In two clinical studies (Studies A and B), adult patients with type 1 diabetes (Study A; n=585, Study B; n=534) were randomized to 28 weeks of basal-bolus treatment with insulin glargine or NPH insulin. Regular human insulin was administered before each meal. Insulin glargine was administered at bedtime. NPH insulin was administered either as once daily at bedtime or in the morning and at bedtime when used twice daily.

In Study A, the average age was 39 years. The majority of patients were White (99%) and 56% were male. The mean BMI was approximately 24.9 kg/m^2. The mean duration of diabetes was 16 years.

In Study B, the average age was 39 years. The majority of patients were White (95%) and 51% were male. The mean BMI was approximately 25.8 kg/m^2. The mean duration of diabetes was 17 years.

In another clinical study (Study C), patients with type 1 diabetes (n=619) were randomized to 16 weeks of basal-bolus treatment with insulin glargine or NPH insulin. Insulin lispro was used before each meal. Insulin glargine was administered once daily at bedtime and NPH insulin was administered once or twice daily. The average age was 39 years. The majority of patients were White (97%) and 51% were male. The mean BMI was approximately 25.6 kg/m^2. The mean duration of diabetes was 19 years.

In these 3 adult studies, insulin glargine and NPH insulin had similar effects on HbA1c (Table 9) with a similar overall rate of severe symptomatic hypoglycemia [see Adverse Reactions (6.1)].

Table 9: Type 1 Diabetes Mellitus – Adults
Treatment duration Treatment in combination with | Study A 28 weeks Regular insulin |  |  | Study B 28 weeks Regular insulin |  | Study C 16 weeks Insulin lispro
Treatment duration Treatment in combination with | Insulin Glargine |  | NPH | Insulin Glargine | NPH | Insulin Glargine | NPH
Number of subjects treated | 292 |  | 293 | 264 | 270 | 310 | 309
HbA1c
Baseline HbA1c | 8.0 |  | 8.0 | 7.7 | 7.7 | 7.6 | 7.7
Adjusted mean change at study end | +0.2 |  | +0.1 | -0.2 | -0.2 | -0.1 | -0.1
Treatment Difference (95% CI) | +0.1 (0.0; + 0.2) |  |  | +0.1 (-0.1; + 0.2) |  | 0.0 (-0.1; + 0.1)
Basal insulin dose
Baseline mean | 21 | 23 |  | 29 | 29 | 28 | 28
Mean change from baseline | -2 | 0 |  | -4 | +2 | -5 | +1
Total insulin dose
Baseline mean | 48 | 52 |  | 50 | 51 | 50 | 50
Mean change from baseline | -1 | 0 |  | 0 | +4 | -3 | 0
Fasting blood glucose (mg/dL)
Baseline mean | 167 | 166 |  | 166 | 175 | 175 | 173
Adj. mean change from baseline | -21 | -16 |  | -20 | -17 | -29 | -12
Body weight (kg)
Baseline mean | 73.2 | 74.8 |  | 75.5 | 75.0 | 74.8 | 75.6
Mean change from baseline | 0.1 | -0.0 |  | 0.7 | 1.0 | 0.1 | 0.5

Pediatric Patients with Type 1 Diabetes

In a randomized, controlled clinical study (Study D), pediatric patients (age range 6 to 15 years) with type 1 diabetes (n=349) were treated for 28 weeks with a basal-bolus insulin regimen where regular human insulin was used before each meal. Insulin glargine was administered once daily at bedtime and NPH insulin was administered once or twice daily. The average age was 11.7 years. The majority of patients were White (97%) and 52% were male. The mean BMI was approximately 18.9 kg/m^2. The mean duration of diabetes was 5 years. Similar effects on HbA1c (Table 10) were observed in both treatment groups [see Adverse Reactions (6.1)].

Table 10: Type 1 Diabetes Mellitus – Pediatric Patients
Treatment duration Treatment in combination with | Study D 28 weeks Regular insulin
 | Insulin Glargine + Regular insulin | NPH + Regular insulin
Number of subjects treated | 174 | 175
HbA1c
Baseline mean | 8.5 | 8.8
Change from baseline (adjusted mean) | +0.3 | +0.3
Difference from NPH (adjusted mean) (95% CI) | 0.0 (-0.2; +0.3)
Basal insulin dose
Baseline mean | 19 | 19
Mean change from baseline | -1 | +2
Total insulin dose
Baseline mean | 43 | 43
Mean change from baseline | +2 | +3
Fasting blood glucose (mg/dL)
Baseline mean | 194 | 191
Mean change from baseline | -23 | -12
Body weight (kg)
Baseline mean | 45.5 | 44.6
Mean change from baseline | 2.2 | 2.5

14.3 Clinical Studies in Adults with Type 2 Diabetes

In a randomized, controlled clinical study (Study E) in 570 adults with type 2 diabetes, insulin glargine was evaluated for 52 weeks in combination with oral antidiabetic medications (a sulfonylurea, metformin, acarbose, or combinations of these drugs). The average age was 60 years old. The majority of patients were White (93%) and 54% were male. The mean BMI was approximately 29.1 kg/m^2. The mean duration of diabetes was 10 years. Insulin glargine administered once daily at bedtime was as effective as NPH insulin administered once daily at bedtime in reducing HbA1c and fasting glucose (Table 11). The rate of severe symptomatic hypoglycemia was similar in insulin glargine and NPH insulin treated patients [see Adverse Reactions (6.1)].

In a randomized, controlled clinical study (Study F), in adult patients with type 2 diabetes not using oral antidiabetic medications (n=518), a basal-bolus regimen of insulin glargine once daily at bedtime or NPH insulin administered once or twice daily was evaluated for 28 weeks. Regular human insulin was used before meals, as needed. The average age was 59 years. The majority of patients were White (81%) and 60% were male. The mean BMI was approximately 30.5 kg/m^2. The mean duration of diabetes was 14 years. Insulin glargine had similar effectiveness as either once- or twice daily NPH insulin in reducing HbA1c and fasting glucose (Table 11) with a similar incidence of hypoglycemia [see Adverse Reactions (6.1)].

In a randomized, controlled clinical study (Study G), adult patients with type 2 diabetes were randomized to 5 years of treatment with once-daily insulin glargine or twice-daily NPH insulin. For patients not previously treated with insulin, the starting dosage of insulin glargine or NPH insulin was 10 units daily. Patients who were already treated with NPH insulin either continued on the same total daily NPH insulin dose or started insulin glargine at a dosage that was 80% of the total previous NPH insulin dosage. The primary endpoint for this study was a comparison of the progression of diabetic retinopathy by 3 or more steps on the Early Treatment Diabetic Retinopathy Study (ETDRS) scale. HbA1c change from baseline was a secondary endpoint. Similar glycemic control in the 2 treatment groups was desired in order to not confound the interpretation of the retinal data. Patients or study personnel used an algorithm to adjust the insulin glargine and NPH insulin dosages to a target fasting plasma glucose ≤100 mg/dL. After the insulin glargine or NPH insulin dosage was adjusted, other antidiabetic agents, including premeal insulin were to be adjusted or added. The average age was 55 years. The majority of patients were White (85%) and 54% were male. The mean BMI was approximately 34.3 kg/m^2. The mean duration of diabetes was 11 years. The insulin glargine group had a smaller mean reduction from baseline in HbA1c compared to the NPH insulin group, which may be explained by the lower daily basal insulin doses in the insulin glargine group (Table 11). The incidences of severe symptomatic hypoglycemia were similar between groups [see Adverse Reactions (6.1)].

Table 11: Type 2 Diabetes Mellitus - Adults
Treatment duration Treatment in combination with | Study E 52 weeks Oral agents |  | Study F 28 weeks Regular insulin |  | Study G 5 years Regular insulin
 | Insulin Glargine | NPH | Insulin Glargine | NPH | Insulin Glargine | NPH
Number of subjects treated | 289 | 281 | 259 | 259 | 513 | 504
HbA1c
Baseline mean | 9.0 | 8.9 | 8.6 | 8.5 | 8.4 | 8.3
Adjusted mean change from baseline | -0.5 | -0.4 | -0.4 | -0.6 | -0.6 | -0.8
Insulin glargine – NPH | -0.1 |  | +0.2 |  | +0.2
95% CI for Treatment difference | (-0.3; +0.1) |  | (0.0; +0.4) |  | (+0.1; +0.4)
Basal insulin dose*
Baseline mean | 14 | 15 | 44.1 | 45.5 | 39 | 44
Mean change from baseline | +12 | +9 | -1 | +7 | +23 | +30
Total insulin dose*
Baseline mean | 14 | 15 | 64 | 67 | 48 | 53
Mean change from baseline | +12 | +9 | +10 | +13 | +41 | +40
Fasting blood glucose (mg/dL)
Baseline mean | 179 | 180 | 164 | 166 | 190 | 180
Adj. mean change from baseline | -49 | -46 | -24 | -22 | -45 | -44
Body weight (kg)
Baseline mean | 83.5 | 82.1 | 89.6 | 90.7 | 100 | 99
Adj. mean change from baseline | 2.0 | 1.9 | 0.4 | 1.4 | 3.7 | 4.8
* In Study G, the baseline dose of basal or total insulin was the first available on-treatment dose prescribed during the study (on visit month 1.5)

14.4 Additional Clinical Studies in Adults with Diabetes Type 1 and Type 2

Different Timing of Insulin Glargine Administration in Diabetes Type 1 and Diabetes Type 2

The safety and efficacy of once daily insulin glargine administered either at pre-breakfast, pre-dinner, or at bedtime were evaluated in a randomized, controlled clinical study in adult patients with type 1 diabetes (Study H; n=378). Patients were also treated with insulin lispro at mealtime. The average age was 41 years. All patients were White (100%) and 54% were male. The mean BMI was approximately 25.3 kg/m^2. The mean duration of diabetes was 17 years.

Insulin glargine administered at pre-breakfast or at pre-dinner (both once daily) resulted in similar reductions in HbA1c compared to that with bedtime administration (see Table 12). In these patients, data are available from 8-point home glucose monitoring. The maximum mean blood glucose was observed just prior to insulin glargine injection regardless of time of administration. In this study, 5% of patients in the insulin glargine-breakfast group discontinued treatment because of lack of efficacy. No patients in the other two groups (pre-dinner, bedtime) discontinued for this reason.

The safety and efficacy of once daily insulin glargine administered pre-breakfast or at bedtime were also evaluated in a randomized, active-controlled clinical study (Study I, n=697) in patients with type 2 diabetes not adequately controlled on oral antidiabetic therapy. All patients in this study also received glimepiride 3 mg daily. The average age was 61 years. The majority of patients were White (97%) and 54% were male. The mean BMI was approximately 28.7 kg/m^2. The mean duration of diabetes was 10 years. Insulin glargine given before breakfast was at least as effective in lowering HbA1c as insulin glargine given at bedtime or NPH insulin given at bedtime (see Table 12).

Table 12 Study of Different Times of Once Daily Insulin Glargine Dosing in Type 1 (Study H) and Type 2 (Study I) Diabetes Mellitus
Treatment duration Treatment in combination with | Study H 24 weeks Insulin lispro |  |  | Study I 24 weeks Glimepiride
 | Insulin Glargine Before Breakfast | Insulin Glargine Before Dinner | Insulin Glargine Bedtime | Insulin Glargine Before Breakfast | Insulin Glargine Bedtime | NPH Bedtime
Number of subjects treated* | 112 | 124 | 128 | 234 | 226 | 227
HbA1c
Baseline mean | 7.6 | 7.5 | 7.6 | 9.1 | 9.1 | 9.1
Mean change from baseline | -0.2 | -0.1 | 0.0 | -1.3 | -1.0 | -0.8
Basal insulin dose (Units)
Baseline mean | 22 | 23 | 21 | 19 | 20 | 19
Mean change from baseline | 5 | 2 | 2 | 11 | 18 | 18
Total insulin dose (Units) | -- | -- | -- | NA† | NA† | NA†
Baseline mean | 52 | 52 | 49 | -- | -- | --
Mean change from baseline | 2 | 3 | 2 | -- | -- | --
Body weight (kg)
Baseline mean | 77.1 | 77.8 | 74.5 | 80.7 | 82 | 81
Mean change from baseline | 0.7 | 0.1 | 0.4 | 3.9 | 3.7 | 2.9
* Intent to treat.
† Not applicable.

Progression of Retinopathy Evaluation in Adults with Diabetes Type 1 and Diabetes Type 2

Insulin glargine was compared to NPH insulin in a 5-year randomized clinical study that evaluated the progression of retinopathy as assessed with fundus photography using a grading protocol derived from the Early Treatment Diabetic Retinopathy Scale (ETDRS). Patients had type 2 diabetes (mean age 55 years) with no (86%) or mild (14%) retinopathy at baseline. Mean baseline HbA1c was 8.4%. The primary outcome was progression by 3 or more steps on the ETDRS scale at study endpoint. Patients with prespecified postbaseline eye procedures (pan-retinal photocoagulation for proliferative or severe nonproliferative diabetic retinopathy, local photocoagulation for new vessels, and vitrectomy for diabetic retinopathy) were also considered as 3-step progressors regardless of actual change in ETDRS score from baseline. Retinopathy graders were blinded to treatment group assignment.

The results for the primary endpoint are shown in Table 13 for both the per-protocol and intent-to-treat populations, and indicate similarity of insulin glargine to NPH in the progression of diabetic retinopathy as assessed by this outcome. In this study, the numbers of retinal adverse events reported for insulin glargine and NPH insulin treatment groups were similar for adult patients with type 1 and type 2 diabetes.

Table 13: Number (%) of Patients with 3 or More Step Progression on ETDRS Scale at Endpoint
 | Insulin Glargine (%) | NPH (%) | Difference*,† (SE) | 95% CI for difference
Per-protocol | 53/374 (14.2%) | 57/363 (15.7%) | -2.0% (2.6%) | -7.0% to +3.1%
Intent-to-Treat | 63/502 (12.5%) | 71/487 (14.6%) | -2.1% (2.1%) | -6.3% to +2.1%
* Difference = Insulin Glargine – NPH.
† Using a generalized linear model (SAS GENMOD) with treatment and baseline HbA1c strata (cutoff 9.0%) as the classified independent variables, and with binomial distribution and identity link function.

The ORIGIN Study of Major Cardiovascular Outcomes in Patients with Established CV Disease or CV Risk Factors

The Outcome Reduction with Initial Glargine Intervention study (i.e., ORIGIN) was an open-label, randomized, 2-by-2, factorial design study. One intervention in ORIGIN compared the effect of insulin glargine to standard care on major adverse cardiovascular (CV) outcomes in 12,537 adults ≥50 years of age with:

- Abnormal glucose levels (i.e., impaired fasting glucose [IFG] and/or impaired glucose tolerance [IGT]) or early type 2 diabetes mellitus and
- Established CV disease or CV risk factors at baseline.

The objective of the study was to demonstrate that insulin glargine use could significantly lower the risk of major CV outcomes compared to standard care. There were two coprimary composite CV endpoints:

- The first coprimary endpoint was the time to first occurrence of a major adverse CV event defined as the composite of CV death, nonfatal myocardial infarction and nonfatal stroke.
- The second coprimary endpoint was the time to the first occurrence of CV death or nonfatal myocardial infarction or nonfatal stroke or revascularization procedure or hospitalization for heart failure.

Patients were randomized to either insulin glargine (N=6,264) titrated to a goal fasting plasma glucose of ≤95 mg/dL or to standard care (N=6,273). Anthropometric and disease characteristics were balanced at baseline. The mean age was 64 years and 8% of patients were 75 years of age or older. The majority of patients were male (65%). Fifty nine percent were White, 25% were Latin, 10% were Asian and 3% were Black or African American. The median baseline BMI was 29 kg/m^2. Approximately 12% of patients had abnormal glucose levels (IGT and/or IFG) at baseline and 88% had type 2 diabetes. For patients with type 2 diabetes, 59% were treated with a single oral antidiabetic drug, 23% had known diabetes but were on no antidiabetic drug and 6% were newly diagnosed during the screening procedure. The mean HbA1c (SD) at baseline was 6.5% (1.0). Fifty-nine percent of the patients had a prior CV event and 39% had documented coronary artery disease or other CV risk factors.

Vital status was available for 99.9% and 99.8% of patients randomized to insulin glargine and standard care respectively at end of study. The median duration of follow-up was 6.2 years (range: 8 days to 7.9 years). The mean HbA1c (SD) at the end of the study was 6.5% (1.1) and 6.8% (1.2) in the insulin glargine and standard care group respectively. The median dose of insulin glargine at end of study was 0.45 U/kg. Eighty-one percent of patients randomized to insulin glargine were using insulin glargine at end of the study. The mean change in body weight from baseline to the last treatment visit was 2.2 kg greater in the insulin glargine group than in the standard care group.

Overall, the incidence of major adverse CV outcomes was similar between groups (see Table 14). All-cause mortality was also similar between groups.

Table 14: Cardiovascular Outcomes in ORIGIN in Patients with Established CV Disease or CV Risk Factors - Time to First Event Analyses
 | Insulin Glargine N=6,264 | Standard Care N=6,273 | Insulin Glargine vs. Standard Care
 | n (Events per 100 PY) | n (Events per 100 PY) | Hazard Ratio (95% CI)
Coprimary endpoints
CV death, nonfatal myocardial infarction, or nonfatal stroke | 1,041 (2.9) | 1,013 (2.9) | 1.02 (0.94, 1.11)
CV death, nonfatal myocardial infarction, nonfatal stroke, hospitalization for heart failure or revascularization procedure | 1,792 (5.5) | 1,727 (5.3) | 1.04 (0.97, 1.11)
Components of coprimary endpoints
CV death | 580 | 576 | 1.00 (0.89, 1.13)
Myocardial Infarction (fatal or nonfatal) | 336 | 326 | 1.03 (0.88, 1.19)
Stroke (fatal or nonfatal) | 331 | 319 | 1.03 (0.89, 1.21)
Revascularizations | 908 | 860 | 1.06 (0.96, 1.16)
Hospitalization for heart failure | 310 | 343 | 0.90 (0.77, 1.05)

In the ORIGIN study, the overall incidence of cancer (all types combined) or death from cancer (Table 15) was similar between treatment groups.

Table 15: Cancer Outcomes in ORIGIN – Time to First Event Analyses
 | Insulin Glargine N=6,264 | Standard Care N=6,273 | Insulin Glargine vs. Standard Care
 | n (Events per 100 PY) | n (Events per 100 PY) | Hazard Ratio (95% CI)
Cancer endpoints
Any cancer event (new or recurrent) | 559 (1.56) | 561 (1.56) | 0.99 (0.88, 1.11)
New cancer events | 524 (1.46) | 535 (1.49) | 0.96 (0.85, 1.09)
Death due to Cancer | 189 (0.51) | 201 (0.54) | 0.94 (0.77, 1.15)

16 HOW SUPPLIED/STORAGE AND HANDLING

16.1 How Supplied

REZVOGLAR (insulin glargine-aglr) injection is supplied as a clear and colorless solution containing 100 units/mL (U-100) available as follows:

REZVOGLAR | NDC number | Package size
3 mL KwikPen single-patient-use prefilled pen | 0002-8980-05 (HP-8980) | 5 pens per carton

Additional Information about REZVOGLAR KwikPen:

- The REZVOGLAR KwikPen prefilled pen dials in 1 unit increments.
- Needles are not included in the packs.

This device is recommended for use with Becton, Dickinson & Company's insulin pen needles which are sold separately.

16.2 Storage

Dispense in the original sealed carton with the enclosed Instructions for Use.

Store unused REZVOGLAR in a refrigerator between 36°F and 46°F (2°C and 8°C). Do not freeze. Discard REZVOGLAR if it has been frozen. Protect REZVOGLAR from direct heat and light.

Storage conditions are summarized in the following table:

 | Not In-Use (unopened) Refrigerated (36°F to 46°F [2°C to 8°C]) | Not In-Use (unopened) Room Temperature (up to 86°F [30°C]) | In-Use (opened) (see temperature below)
3 mL single-patient-use KwikPena prefilled pen | Until expiration date | 28 days | 28 days Room temperature only (Do not refrigerate)
a When stored at room temperature, REZVOGLAR KwikPen can only be used for a total of 28 days including both not in-use (unopened) and in-use (opened) storage time.

17 PATIENT COUNSELING INFORMATION

Advise the patient to read the FDA-approved patient labeling (Patient Information and Instructions for Use).

Never Share a REZVOGLAR KwikPen Prefilled Pen Between Patients

Advise patients that they must never share a REZVOGLAR KwikPen with another person, even if the needle is changed. Sharing carries a risk for transmission of blood-borne pathogens [see Warnings and Precautions (5.1)].

Hyperglycemia or Hypoglycemia

Inform patients that hypoglycemia is the most common adverse reaction with insulin. Inform patients of the symptoms of hypoglycemia (e.g., impaired ability to concentrate and react). This may present a risk in situations where these abilities are especially important, such as driving or operating other machinery. Advise patients who have frequent hypoglycemia or reduced or absent warning signs of hypoglycemia to use caution when driving or operating machinery [see Warnings and Precautions (5.3)].

Advise patients that changes in insulin regimen can predispose to hyperglycemia or hypoglycemia and that changes in insulin regimen should be made under close medical supervision [see Warnings and Precautions (5.2)].

Hypoglycemia Due to Medication Errors

Instruct patients to always check the insulin label before each injection to reduce the risk of a medication error [see Warnings and Precautions (5.4)].

Hypersensitivity Reactions

Advise patients that hypersensitivity reactions have occurred with insulin glargine products. Inform patients about the symptoms of hypersensitivity reactions [see Warnings and Precautions (5.5)].

Manufactured by:
Eli Lilly and Company, Indianapolis, IN 46285, USA
US License Number 1891

Copyright © 2021, 2024, Eli Lilly and Company. All rights reserved.

REZ-0003-USPI-20240809

PATIENT INFORMATION
REZVOGLARTM KWIKPEN® (REHZ-voh-glahr)
(insulin glargine-aglr) injection for subcutaneous use, 100 Units/mL (U-100)

Do not share your REZVOGLAR™ KwikPen® with other people, even if the needle has been changed. You may give other people a serious infection, or get a serious infection from them.

What is REZVOGLAR?
REZVOGLAR is a long-acting man-made insulin used to control high blood sugar in adults and children with diabetes mellitus. REZVOGLAR is not for use to treat diabetic ketoacidosis.

Who should not use REZVOGLAR?
Do not use REZVOGLAR if you:

- are having an episode of low blood sugar (hypoglycemia).
- have an allergy to insulin glargine products or any of the ingredients in REZVOGLAR. See the end of this Patient Information leaflet for a complete list of ingredients in REZVOGLAR.

What should I tell my healthcare provider before using REZVOGLAR?
Before using REZVOGLAR, tell your healthcare provider about all your medical conditions including if you:

- have liver or kidney problems.
- take other medicines, especially ones called TZDs (thiazolidinediones).
- have heart failure or other heart problems. If you have heart failure, it may get worse while you take TZDs with REZVOGLAR.
- are pregnant, planning to become pregnant, or are breastfeeding. It is not known if REZVOGLAR may harm your unborn baby or breastfeeding baby.

Tell your healthcare provider about all the medicines you take including prescription and over-the-counter medicines, vitamins, and herbal supplements.
Before you start using REZVOGLAR, talk to your healthcare provider about low blood sugar and how to manage it.

How should I use REZVOGLAR KwikPen?

- Read the detailed Instructions for Use that come with your REZVOGLAR KwikPen single-patient-use prefilled pen.
- Use REZVOGLAR exactly as your healthcare provider tells you to. Your healthcare provider should tell you how much REZVOGLAR to use and when to use it.
- Know the amount of REZVOGLAR you use. Do not change the amount of REZVOGLAR you use unless your healthcare provider tells you to.
- Check your insulin label each time you give your injection to make sure you are using the correct insulin.
- The dose indicator on your pen shows your dose of REZVOGLAR. Do not make any dose changes unless your healthcare provider tells you to.
- Do not use a syringe to remove REZVOGLAR from your KwikPen disposable prefilled pen.
- Do not re-use needles. Always use a new needle for each injection. Re-use of needles increases your risk of having blocked needles, which may cause you to get the wrong dose of REZVOGLAR. Using a new needle for each injection lowers your risk of getting an infection. If your needle is blocked, follow the instructions in Step 3 of the Instructions for Use.
- You may take REZVOGLAR at any time during the day but you must take it at the same time every day.
- REZVOGLAR is injected under the skin (subcutaneously) of your upper legs (thighs), upper arms, or stomach area (abdomen).
- Do not use REZVOGLAR in an insulin pump or inject REZVOGLAR into your vein (intravenously).
- Change (rotate) your injection sites within area you chose with each dose to reduce your risk of getting lipodystrophy (pits in skin or thickened skin) and localized cutaneous amyloidosis (skin with lumps) at the injection sites.
  - Do not use the exact same spot for each injection.
  - Do not inject where the skin has pits, is thickened, or has lumps.
  - Do not inject where skin is tender, bruised, scaly or hard, or into scars or damaged skin.
- Do not mix REZVOGLAR with any other type of insulin or liquid medicine.
- Check your blood sugar levels. Ask your healthcare provider what your blood sugar should be and when you should check your blood sugar levels.

Keep REZVOGLAR and all medicines out of the reach of children.

Your dose of REZVOGLAR may need to change because of:

- a change in level of physical activity or exercise, weight gain or loss, increased stress, illness, change in diet, or because of the medicines you take.

What should I avoid while using REZVOGLAR?
While using REZVOGLAR do not:

- drive or operate heavy machinery, until you know how REZVOGLAR affects you.
- drink alcohol or use over-the-counter medicines that contain alcohol.

What are the possible side effects of REZVOGLAR and other insulins?
REZVOGLAR may cause serious side effects that can lead to death, including:

- low blood sugar (hypoglycemia). Signs and symptoms that may indicate low blood sugar include:
  - dizziness or light-headedness, sweating, confusion, headache, blurred vision, slurred speech, shakiness, fast heartbeat, anxiety, irritability or mood change, hunger.
- severe allergic reaction (whole body reaction). Get medical help right away if you have any of these signs or symptoms of a severe allergic reaction:
  - a rash over your whole body, trouble breathing, a fast heartbeat, or sweating.
- low potassium in your blood (hypokalemia).
- heart failure. Taking certain diabetes pills called TZDs (thiazolidinediones) with REZVOGLAR may cause heart failure in some people. This can happen even if you have never had heart failure or heart problems before. If you already have heart failure it may get worse while you take TZDs with REZVOGLAR. Your healthcare provider should monitor you closely while you are taking TZDs with REZVOGLAR. Tell your healthcare provider if you have any new or worse symptoms of heart failure including:
  - shortness of breath, swelling of your ankles or feet, sudden weight gain.

Treatment with TZDs and REZVOGLAR may need to be changed or stopped by your healthcare provider if you have new or worse heart failure.
Get emergency medical help if you have:

- trouble breathing, shortness of breath, fast heartbeat, swelling of your face, tongue, or throat, sweating, extreme drowsiness, dizziness, confusion.

The most common side effects of REZVOGLAR include:

- low blood sugar (hypoglycemia), weight gain; allergic reactions, including reactions at your injection site, skin thickening or pits at the injection site (lipodystrophy).

These are not all the possible side effects of REZVOGLAR. Call your doctor for medical advice about side effects. You may report side effects to FDA at 1-800-FDA-1088.

General information about the safe and effective use of REZVOGLAR.
Medicines are sometimes prescribed for purposes other than those listed in a Patient Information leaflet. Do not use REZVOGLAR for a condition for which it was not prescribed. Do not give REZVOGLAR to other people, even if they have the same symptoms that you have. It may harm them.
This Patient Information leaflet summarizes the most important information about REZVOGLAR. If you would like more information, talk with your healthcare provider. You can ask your healthcare provider or pharmacist for information about REZVOGLAR that is written for healthcare professionals. For more information about REZVOGLAR call 1-800-545-5979 or go to the website www.rezvoglar.com.

What are the ingredients in REZVOGLAR?

- Active ingredient: insulin glargine-aglr
- 3 mL KwikPen prefilled pen inactive ingredients: glycerin, metacresol, zinc, and Water for Injection, USP.

Hydrochloric acid and/or sodium hydroxide may be added to adjust the pH.

Patient Information revised: Nov 2022
Manufactured by:
Eli Lilly and Company, Indianapolis, IN 46285 USA
US License Number 1891
Copyright © 2021, 2022, Eli Lilly and Company. All rights reserved.

This Patient Information has been approved by the U.S. Food and Drug Administration.

REZ-0002-PPI-20221116

KwikPen Instructions for Use

INSTRUCTIONS FOR USE

REZVOGLARTM KwikPen® (REHZ-voh-glahr)

(insulin glargine-aglr)

injection, for subcutaneous use

3 mL Single-Patient-Use PREFILLED-PEN: 100 units/mL (U-100)

Read these Instructions for Use before you start taking the REZVOGLAR KwikPen (“Pen”) and each time you get a new REZVOGLAR KwikPen. There may be new information. This information does not take the place of talking to your healthcare provider about your medical condition or your treatment.

Do not share your REZVOGLAR KwikPen with other people, even if the needle has been changed. You may give other people a serious infection, or get a serious infection from them.

People who are blind or have vision problems should not use REZVOGLAR KwikPen prefilled pen without help from a person trained to use REZVOGLAR KwikPen prefilled pen.

REZVOGLAR KwikPen is a disposable prefilled pen used to inject REZVOGLAR. Each REZVOGLAR KwikPen has 300 units of insulin which can be used for multiple injections. You can select doses from 1 to 80 units in steps of 1 unit. The Pen plunger moves with each dose, but you may not notice that it moves. The plunger will only move to the end of the cartridge when 300 units of REZVOGLAR have been given.

Important Information You Need to Know Before Injecting REZVOGLAR

- Do not use your Pen if it is damaged or if you are not sure that it is working properly.
- Do not use a syringe to remove REZVOGLAR from your Pen.
- Do not reuse Needles. If you do, you might get the wrong dose of REZVOGLAR and/or increase the chance of getting an infection.
- Always perform a safety test (prime the REZVOGLAR KwikPen) (see Step 3).
- Always carry a spare Pen and spare Needles in case of loss or damage.
- Change (rotate) your injection sites within the area you choose for each dose (see “Places to inject”).

Learn to Inject

- Talk with your healthcare provider about how to inject before using your Pen.
- Ask for help if you have problems handling the Pen, for example if you have problems with your sight.
- Read all these instructions before using your Pen. If you do not follow all these instructions, you may get too much or too little insulin.

Need Help?

If you have any questions about your Pen or about diabetes, ask your healthcare provider, or go to www.rezvoglar.com or call Eli Lilly and Company at 1-800-545-5979.

Extra Items You Will Need

- a new sterile Pen Needle (see Step 2).
- an alcohol swab.
- a puncture-resistant container for used Needles and Pens (See "Throwing your Pen away").

Places to inject

- Inject your insulin exactly as your healthcare provider has shown you.
- Inject your insulin under the skin (subcutaneously) of your upper legs (thighs), upper arms, or stomach area (abdomen).
- Change (rotate) your injection sites within the area you choose for each dose to reduce your risk of getting lipodystrophy (pits in skin or thickened skin) and localized cutaneous amyloidosis (skin with lumps) at the injection sites.
- Do not inject where the skin has pits, is thickened, or has lumps.
- Do not inject where the skin is tender, bruised, scaly or hard, or into scars or damaged skin.
- Do not try to change your dose while injecting.

Get to know your Pen

Step 1: Check your Pen

Take a new Pen out of the refrigerator at least 1 hour before you inject. Cold insulin is more painful to inject.

1A Check the name and expiration date on the label of your Pen. The REZVOGLAR KwikPen is light grey with a light grey Dose Knob that has a green ring on the end. The label on the Pen is light grey with green color bars.

- Make sure you have the correct insulin.

- Do not use your Pen after the expiration date.

1B Pull off the Pen Cap.

1C Check that the insulin is clear.

- Do not use the Pen if the insulin looks cloudy, colored or contains particles.

1D Wipe the Rubber Seal with an alcohol swab.

If you have other injector pens:

- Making sure you have the correct medicine is especially important if you have other injector pens.

Step 2: Attach a new Needle

- Do not re-use Needles. Always use a new sterile Needle for each injection. This helps stop blocked Needles, contamination, and infection.

Only use Needles that are compatible with REZVOGLAR KwikPen. Becton, Dickinson and Company (BD) Pen Needles are recommended. These are sold separately. Contact your healthcare provider for further information.

2A Take a new Needle and peel off the Paper Tab.

2B Keep the Needle straight and screw it onto the Pen until fixed. Do not over-tighten.

2C Pull off the Outer Needle Shield. Keep this for later.

2D Pull off the Inner Needle Shield and throw away.

Handling Needles

- Take care when handling Needles to prevent needle-stick injury and cross-infection.

Step 3: Do a safety test (Prime your REZVOGLAR KwikPen)

Always do a safety test (prime) before each injection to:

- Check your Pen and the Needle to make sure they are working properly.
- Make sure that you get the correct REZVOGLAR dose.

3A Select 2 units by turning the Dose Knob until the Dose Indicator is at the 2 mark.

3B Press the Dose Knob all the way in.

When insulin comes out of the Needle tip, your Pen is working correctly:

If no insulin appears:

- You may need to repeat this step up to 4 times before seeing insulin.
- If no insulin comes out after the fourth time, the Needle may be blocked. If this happens:
  - change the Needle (see Step 6 and Step 2),
  - then repeat the safety test (prime) (Step 3).
- Do not use your Pen if there is still no insulin coming out of the Needle tip. Use a new Pen.
- Do not use a syringe to remove insulin from your Pen.

If you see air bubbles:

- You may see air bubbles in the insulin. This is normal, they will not harm you.

Step 4: Select the dose

Do not select a dose or press the Dose Knob without a Needle attached. This may damage your Pen.

4A Make sure a Needle is attached and the dose is set to "0".

4B Turn the Dose Knob until the Dose Indicator lines up with your dose.

- If you turn past your dose, you can turn back down.
- The Dose Knob clicks as you turn it. Do not dial your dose by counting the clicks because you may dial the wrong dose.
- If there are not enough units left in your Pen for your dose, the Dose Indicator will stop at the number of units left.
- If you cannot select your full prescribed dose, use a new Pen or inject the remaining units and use a new Pen to complete your dose.

How to read the Dose Window

Even numbers are shown in line with Dose Indicator.

(Example: 12 units shown in the Dose Window)

Odd numbers, after the number 1, are shown as a line between even numbers.

(Example: 25 units shown in the Dose Window)

Units of REZVOGLAR in your Pen:

- Your Pen contains a total of 300 units of REZVOGLAR. You can select doses from 1 to 80 in steps of 1 unit. Each Pen contains more than 1 dose.
- You can see roughly how many units of insulin are left by looking at where the Plunger is on the insulin scale.

Step 5: Injecting Your REZVOGLAR Dose

If you find it hard to press the Dose Knob in, do not force it as this may break your Pen. See the section below for help.

5A Choose a place to inject as shown in the picture above.

5B Push the Needle into the skin as shown by your healthcare provider.

Do not touch the Dose Knob yet.

5C Place your thumb on the Dose Knob. Then press all the way in and hold.

5D Keep the Dose Knob held in and when you see "0" in the Dose Window, slowly count to 5.

- This will make sure you get your full dose.
- Do not try to inject your insulin by turning the Dose Knob. You will not receive your insulin by turning the Dose Knob.

5E After holding and slowly counting to 5, release the Dose Knob. Then remove the Needle from your skin.

- If you do not see “0” in the Dose Window, you did not receive your full dose. Do not redial. Insert the needle into your skin and finish your injection.
- If you still do not think you received the full amount you dialed for your injection, do not start over or repeat the injection. Monitor your blood glucose and call your healthcare provider for further instructions.

If you find it hard to press the Dose Knob in:

- Change the Needle (see Step 6 and Step 2) then do a safety test (prime the Pen) (see Step 3).
- If you still find it hard to press in, get a new Pen.
- Do not use a syringe to remove insulin from your Pen.

Step 6: Remove the Needle

- Take care when handling Needles to prevent needle-stick injury and cross-infection.
- Do not put the Inner Needle Shield back on.

6A Leave the Outer Needle Shield on a flat surface. Using one hand, scoop the Outer Needle Shield straight onto the Needle. When the tip is covered, lift the Needle and Pen. Then push firmly on.

6B Grip and squeeze the widest part of the Outer Needle Shield. Turn your Pen several times with your other hand to remove the Needle.

- Try again if the Needle does not come off the first time.

6C Throw away the used Needle in a puncture-resistant container (see "Throwing your Pen away" at the end of this Instructions for Use).

6D Put your Pen Cap back on

- Do not put the Pen back in the refrigerator.

Storing the REZVOGLAR KwikPen

Before first use

- Keep new Pens in the refrigerator between 36°F to 46°F (2°C to 8°C).
- Do not freeze. Do not use REZVOGLAR if it has been frozen.
- Unused Pens may be used until the expiration date printed on the Label, if the Pen has been kept in the refrigerator.

After first use

- Keep your Pen at room temperature below 86°F (30°C).
- Keep your Pen away from heat or light.
- Store your Pen with the Pen Cap on.
- Do not put your Pen back in the refrigerator.
- Do not store your Pen with the Needle attached.
- Keep out of the reach of children.
- Only use your Pen for up to 28 days after its first use. Throw away the REZVOGLAR KwikPen you are using after 28 days, even if it still has insulin left in it.

Caring for Your REZVOGLAR KwikPen

Handle your Pen with care

- Do not drop your Pen or knock it against hard surfaces.
- If you think that your Pen may be damaged, do not try to fix it. Use a new one.

Protect your Pen from dust and dirt

- You can clean the outside of your Pen by wiping it with a damp cloth (water only). Do not soak, wash or lubricate your Pen. This may damage it.

Throwing your Pen away

- The used REZVOGLAR KwikPen may be thrown away in your household trash after you have removed the Needle.
- Put the used Needle in an FDA-cleared sharps disposal container right away after use. Do not throw away (dispose of) the used Needles in your household trash.
- If you do not have a FDA-cleared sharps disposal container, you may use a household container that is:
  - made of a heavy-duty plastic,
  - can be closed with a tight-fitting, puncture-resistant lid, without sharps being able to come out,
  - upright and stable during use,
  - leak-resistant, and
  - properly labeled to warn of hazardous waste inside the container.
- When your sharps disposal container is almost full, you will need to follow your community guidelines for the right way to dispose of your sharps disposal container. There may be state or local laws about how you should throw away used Needles and syringes. For more information about safe sharps disposal, and for specific information about sharps disposal in the state that you live in, go to the FDA’s website at: http://www.fda.gov/safesharpsdisposal.
- Do not dispose of your used sharps disposal container in your household trash unless your community guidelines permit this. Do not recycle your used sharps disposal container.

This Instructions for Use has been approved by the U.S. Food and Drug Administration.

Manufactured by:

Eli Lilly and Company

Indianapolis, IN 46285, USA

US License Number 1891

Copyright © 2021, 2022, Eli Lilly and Company. All rights reserved.

REZVOGLARTM and REZVOGLARTM KwikPen® are trademarks of Eli Lilly and Company.

Instructions for Use revised: Nov 2022

REZKP-0002-IFU-20221116

PACKAGE CARTON – REZVOGLAR Tempo Pen 80 UNIT PEN

Dispense in this sealed carton.

NDC 0002-8980-05

REZVOGLAR™

KwikPen®

(insulin glargine-aglr) injection

For Single Patient Use Only

100 units per mL (U-100)

For subcutaneous use only

Can inject from 1 to 80 units in a single injection

5 x 3 mL prefilled pens

prefilled insulin delivery device

Rx only

Read REZVOGLAR™ KwikPen® Instructions for Use.

NEEDLES NOT INCLUDED

This device is recommended for use with Becton, Dickinson & Company's insulin pen needles.

Lilly